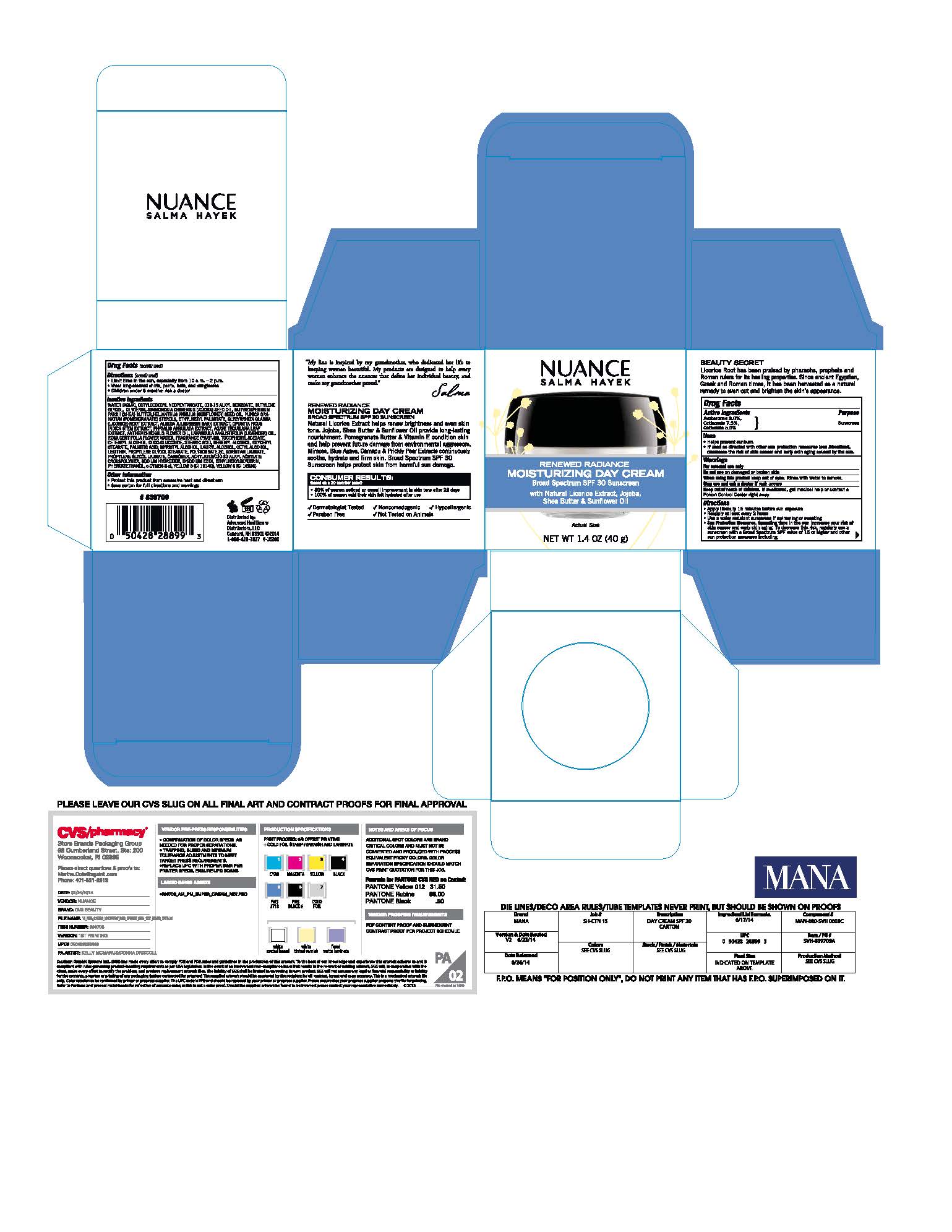 DRUG LABEL: NUANCE Salma Hayek Renewed Radiance Moisturizing Day Cream Broad Spectrum SPF 30 Sunscreen
NDC: 59779-777 | Form: LOTION
Manufacturer: CVS Pharmacy, Inc
Category: otc | Type: HUMAN OTC DRUG LABEL
Date: 20170118

ACTIVE INGREDIENTS: AVOBENZONE 3 g/100 g; OCTINOXATE 7.5 g/100 g; OCTISALATE 5 g/100 g
INACTIVE INGREDIENTS: WATER; OCTYLDODECYL NEOPENTANOATE; BUTYLENE GLYCOL; MICA; TITANIUM DIOXIDE; GLYCERIN; SIMMONDSIA CHINENSIS SEED; SHEA BUTTER; STEARIC ACID; BEHENYL BENZOATE; GLYCERYL STEARATE SE; MYRISTYL ALCOHOL; LAURYL ALCOHOL; CETYL ALCOHOL; PALMITIC ACID; COCO GLUCOSIDE; .ALPHA.-TOCOPHEROL ACETATE; TETRAHEXYLDECYL ASCORBATE; PRUNUS ARMENIACA LEAF; CARICA PAPAYA LEAF; CYMBOPOGON SCHOENANTHUS OIL; AESCULUS HIPPOCASTANUM LEAF; ALOE VERA LEAF; POLYSORBATE 20; SORBITAN OLIVATE; PROPYLENE GLYCOL STEARATE; CARBOMER 940; SODIUM HYDRIDE; PROPYLENE GLYCOL LAURATES; ETHYLHEXYLGLYCERIN; DISODIUM EDTA-COPPER; PHENOXYETHANOL; O-CYMEN-5-OL; BENZYL ALCOHOL; BENZYL SALICYLATE; BUTYLPHENYL METHYLPROPIONAL

DRUG FACTS

Active Ingredients

Avobenzone 3.00%

Octinoxate 7.50%

Octisalate 5.0%

Use

Helps prevent sunburn. If used as directed with other sun protection measures, helps decrease the risk of skin cancer and early signs of aging caused by the sun.

Warnings

- For external use only
- Do not use on damaged or broken skin
- When using this product keep out of eyes. Rinse with water to remove
- Stop use and ask a docor if rash occurs
- Keep out of reach of children. If swalled, get medical help or contact a Poison Control Center right away.

Directions

- Apply liberally 15 minutes before sun exposure
- Use water resistant sunscreen if swimming or sweathing
- Reapply at least every 2 hours
- Children under 6 months: ask a doctor
- Sun Protection Measures: Spending time in the sun decreases risk of skin cancer and early again. To decrease this risk, regulaory use a sunscreen with a Broad Spectrum SPF value of 15 or higher and other sun protection measures including: Limit time in the sun especially from 10:00 am - 2:00 pm. Wear long sleeved shirts, pants, hats and sunglasses.

Inactive Ingredients

Water (Aqua, Eau), Octyldodecyl Neopentanoate, C12-15 Alkyl Benzoate, Butylene Glycol, Mica, Titanium Dioxide (CI 77891), Glycerin, Simmondsia Chinensis Seed Oil, Butyrospermum Parkii (Shea) Butter, Hexapeptide-33, Stearic Acid, Behenyl Alcohol, Glyceryl Stearate, Lecithin,Myristyl Alcohol, Lauryl Alcohol, Cetyl Alcohol, Palmitic Acid, Cetearyl Alcohol, Coco-Glucoside, Tocopheryl Acetate, Tetrahexyldecyl Ascorbate, Prunus Armeniaca Kernel Oil, Carica Papaya Fruit Extract, Cymbopogon Schoenanthus Extract, Aesculus Hippocastanum Seed Extract, Aloe Barbadensis Leaf Extract, Polysorbate 20, Sorbitan Laurate, Propylene Glycol Stearate, Acrylates/C10-30 Alkyl Acrylate Crosspolymer, Carbomer, Sodium Hydroxide, Propylene Glycol Laurate, Ethylhexylglycerin, Disodium Edta, Phenoxyethanol, o-Cymen-5-Ol, Fragrance (Parfum), Benzyl Alcohol, Benzyl Salicylate, Butylphenyl Methylpropional, d-Limonene

Other Information

Protect this product form excessive heat and direct sun